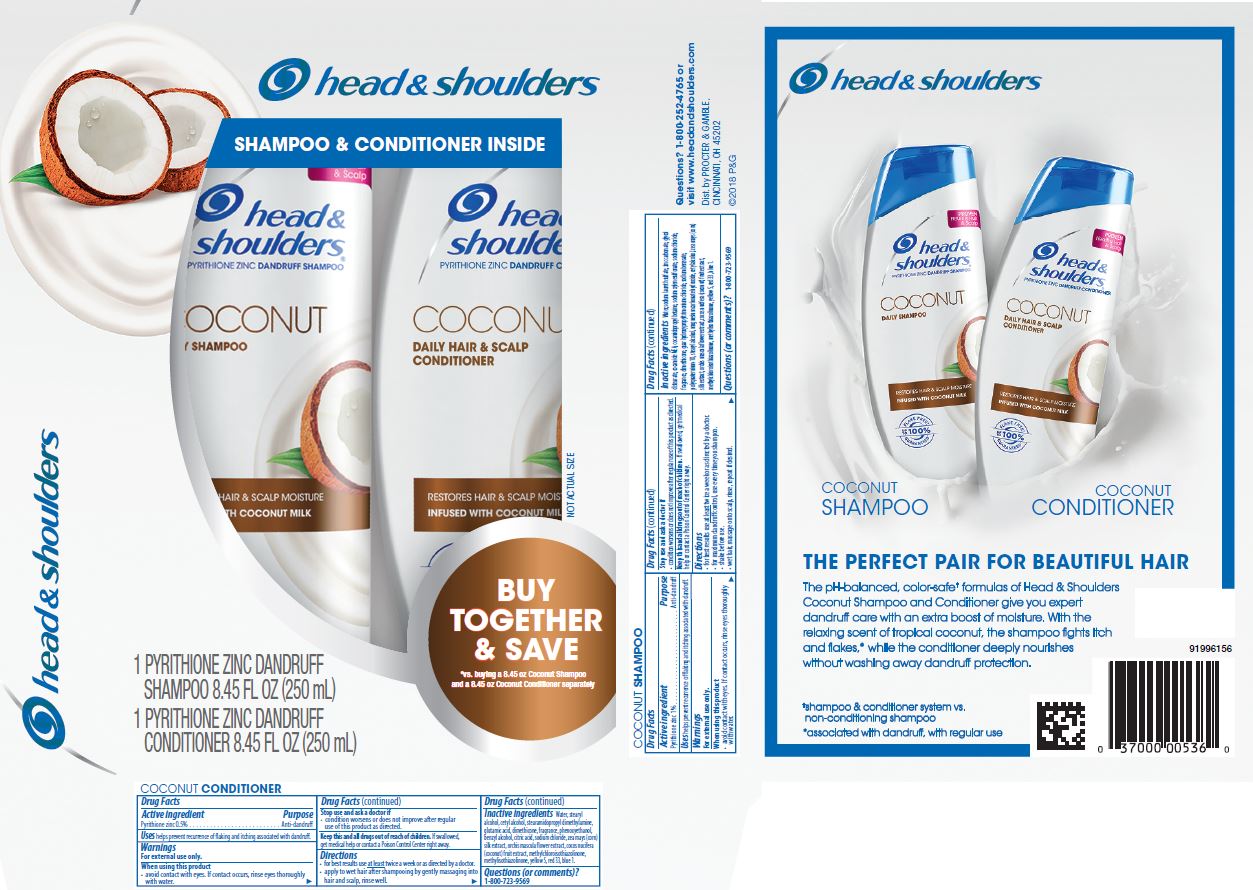 DRUG LABEL: Head and Shoulders Coconut Kit
NDC: 69423-396 | Form: KIT | Route: TOPICAL
Manufacturer: The Procter & Gamble Manufacturing Company
Category: otc | Type: HUMAN OTC DRUG LABEL
Date: 20251216

ACTIVE INGREDIENTS: PYRITHIONE ZINC 1 g/100 mL; PYRITHIONE ZINC 0.5 g/100 mL
INACTIVE INGREDIENTS: STEARYL ALCOHOL; ORCHIS MASCULA FLOWER; COCO MONOETHANOLAMIDE; POLYQUATERNIUM-10 (30000 MPA.S AT 2%); FD&C BLUE NO. 1; MAGNESIUM CARBONATE HYDROXIDE; METHYLCHLOROISOTHIAZOLINONE; METHYLISOTHIAZOLINONE; D&C RED NO. 33; WATER; SODIUM LAURETH-3 SULFATE; GLYCOL DISTEARATE; ZINC CARBONATE; SODIUM CHLORIDE; SODIUM XYLENESULFONATE; COCAMIDOPROPYL BETAINE; DIMETHICONE; SODIUM BENZOATE; COCONUT; CORN SILK; GUAR HYDROXYPROPYLTRIMONIUM CHLORIDE (1.7 SUBSTITUENTS PER SACCHARIDE); FD&C YELLOW NO. 5; CETYL ALCOHOL; STEARYL ALCOHOL; WATER; CETYL ALCOHOL; STEARAMIDOPROPYL DIMETHYLAMINE; GLUTAMIC ACID; PHENOXYETHANOL; BENZYL ALCOHOL; SODIUM CHLORIDE; METHYLISOTHIAZOLINONE; DIMETHICONE; CITRIC ACID MONOHYDRATE; METHYLCHLOROISOTHIAZOLINONE; ORCHIS MASCULA FLOWER; COCONUT; CORN SILK

Head and Shoulders® Coconut Kit

head & shoulders
COCONUT SHAMPOO

Drug Facts

Active ingredient

Pyrithione zinc 1%

Purpose

Anti-dandruff

Uses

helps prevent recurrence of flaking and itching associated with dandruff.

Warnings

For external use only.

When using this product

- avoid contact with eyes. If contact occurs, rinse eyes thoroughly with water.

Stop use and ask a doctor if

- condition worsens or does not improve after regular use of this product as directed.

KEEP OUT OF REACH OF CHILDREN

Keep this and all drugs out of reach of children.

If swallowed, get medical help or contact a Poison Control Center right away.

Directions

- for best results use at least twice a week or as directed by a doctor.
- for maximum dandruff control, use every time you shampoo.
- shake before use.
- wet hair, massage onto scalp, rinse, repeat if desired.

Inactive ingredients

Water, sodium laureth sulfate, zinc carbonate, glycol distearate, cocamide MEA, cocamidopropyl betaine, sodium xylenesulfonate, sodium chloride, fragrance, dimethicone, guar hydroxypropyltrimonium chloride, sodium benzoate, polyquaternium-10, stearyl alcohol, magnesium carbonate hydroxide, cetyl alcohol, zea mays (corn) silk extract, orchis mascula flower extract, cocos nucifera (coconut) fruit extract, methylchloroisothiazolinone, methylisothiazolinone, yellow5, red 33, blue1.

Questions (or comments)?

1-800-723-9569

head & shoulders
COCONUT CONDITIONER

Drug Facts

Active ingredient

Pyrithione zinc 0.5%

Purpose

Anti-dandruff

Uses

helps prevent recurrence of flaking and itching associated with dandruff.

Warnings

For external use only.

When using this product

- avoid contact with eyes. If contact occurs, rinse eyes thoroughly with water.

Stop use and ask a doctor if

- condition worsens or does not improve after regular use of this product as directed.

KEEP OUT OF REACH OF CHILDREN

Keep this and all drugs out of reach of children.

If swallowed, get medical help or contact a Poison Control Center right away.

Directions

- for best results use at least twice a week or as directed by a doctor.
- apply to wet hair after shampooing by gently massaging into hair and scalp, rinse well.

Inactive ingredients

Water, stearyl alcohol, cetyl alcohol, stearamidopropyl dimethylamine, glutamic acid, dimethicone, fragrance, phenoxyethanol, benzyl alcohol, citric acid, sodium chloride, zea mays (corn) silk extract, orchis mascula flower extract, cocos nucifera (coconut) fruit extract, methylchloroisothiazolinone, methylisothiazolinone, yellow 5, red 33, blue 1.

Questions (or comments)?

1-800-723-9569

Dist. by PROCTER & GAMBLE,
CINCINNATI, OH 45202

PRINCIPAL DISPLAY PANEL - Kit Carton

head & shoulders ®

Shampoo & Conditioner Inside

head & shoulders ®

pyrithione zinc dandruff shampoo

COCONUT

DAILY SHAMPOO

head & shoulders ®

pyrithione zinc dandruff conditioner

COCONUT

DAILY HAIR & SCALP

CONDITIONER

1 PYRITHIONE ZINC DANDRUFF

SHAMPOO 8.45 FL OZ (250 mL)

1 PYRITHIONE ZINC DANDRUFF

CONDITIONER 8.45 FL OZ (250 mL)